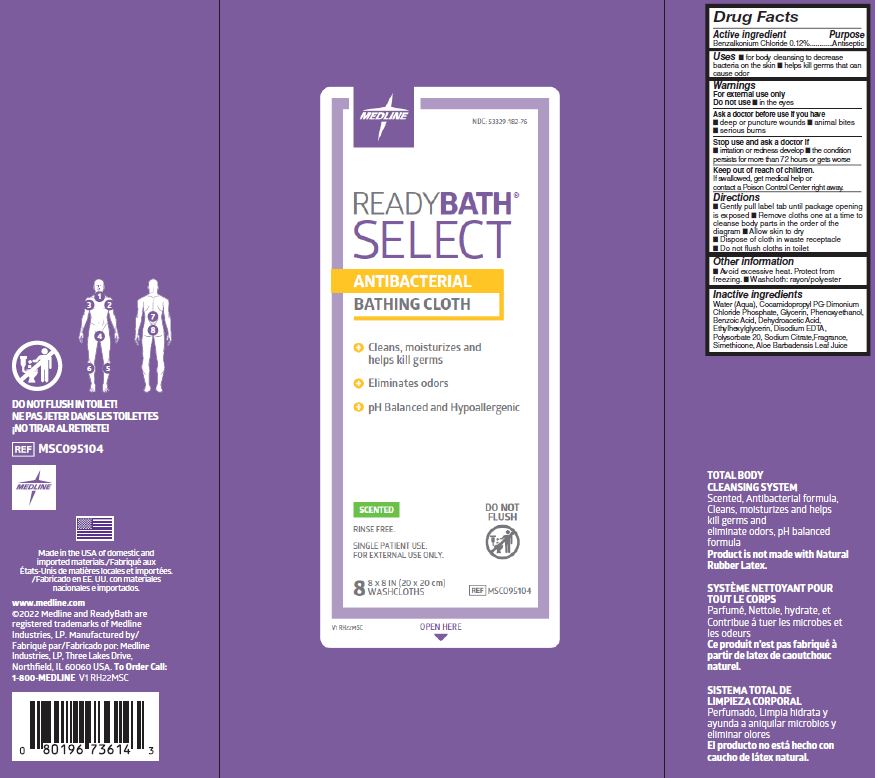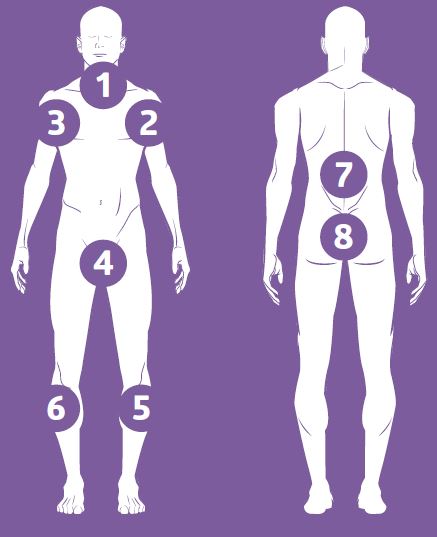 DRUG LABEL: ReadyBath Select
NDC: 53329-182 | Form: CLOTH
Manufacturer: Medline Industries, LP
Category: otc | Type: HUMAN OTC DRUG LABEL
Date: 20250611

ACTIVE INGREDIENTS: BENZALKONIUM CHLORIDE 0.12 g/100 g
INACTIVE INGREDIENTS: GLYCERIN; PHENOXYETHANOL; DEHYDROACETIC ACID; COCAMIDOPROPYL PG-DIMONIUM CHLORIDE PHOSPHATE; BENZOIC ACID; ETHYLHEXYLGLYCERIN; DIMETHICONE; ALOE VERA LEAF; SODIUM CITRATE; EDETATE DISODIUM; POLYSORBATE 20; WATER

182 ReadyBath SELECT (scented)

Active ingredient

Benzalkonium chloride 0.12%

Purpose

Antiseptic

Uses

- for body cleansing to decrease bacteria on the skin
- helps kill germs that can cause odor

Warnings

For external use only

Do not use

- in the eyes

Ask a doctor before use if you have

- deep or puncture wounds
- animal bites
- serious burns

Stop use and ask a doctor if

- irritation and redness develop
- the condition persists for more than 72 hours or gets worse

Keep out of reach of children.

If swallowed get medical help or contact a Poison Control Center right away.

Directions

- gently pull label tab until package opening is exposed
- remove cloths one at a time to cleanse body parts in the order of the diagram
- allow skin to dry
- dispose of cloth in waste receptacle
- do not flush cloths in toilet

Other information

- avoid excessive heat,protect from freezing
- washcloth: rayon/polyester

Inactive ingredients

water (aqua) , cocamidopropyl PG-dimonium chloride phosphate, glycerin, phenoxyethanol, benzoic acid, dehydroacetic acid, ethylhexylglycerin, disodium EDTA, polysorbate 20, sodium citrate, fragrance, simethicone, aloe barbadensis leaf juice

Manufacturing Information

Manufactured by:

Medline Industries, LP

Three Lakes Drive, Northfield, IL 60093 USA

Made in USA with domestic and foreign materials

www.medline.com

1-800-MEDLINE (633-5463)

REF: MSC095104

V1 RH22MSC